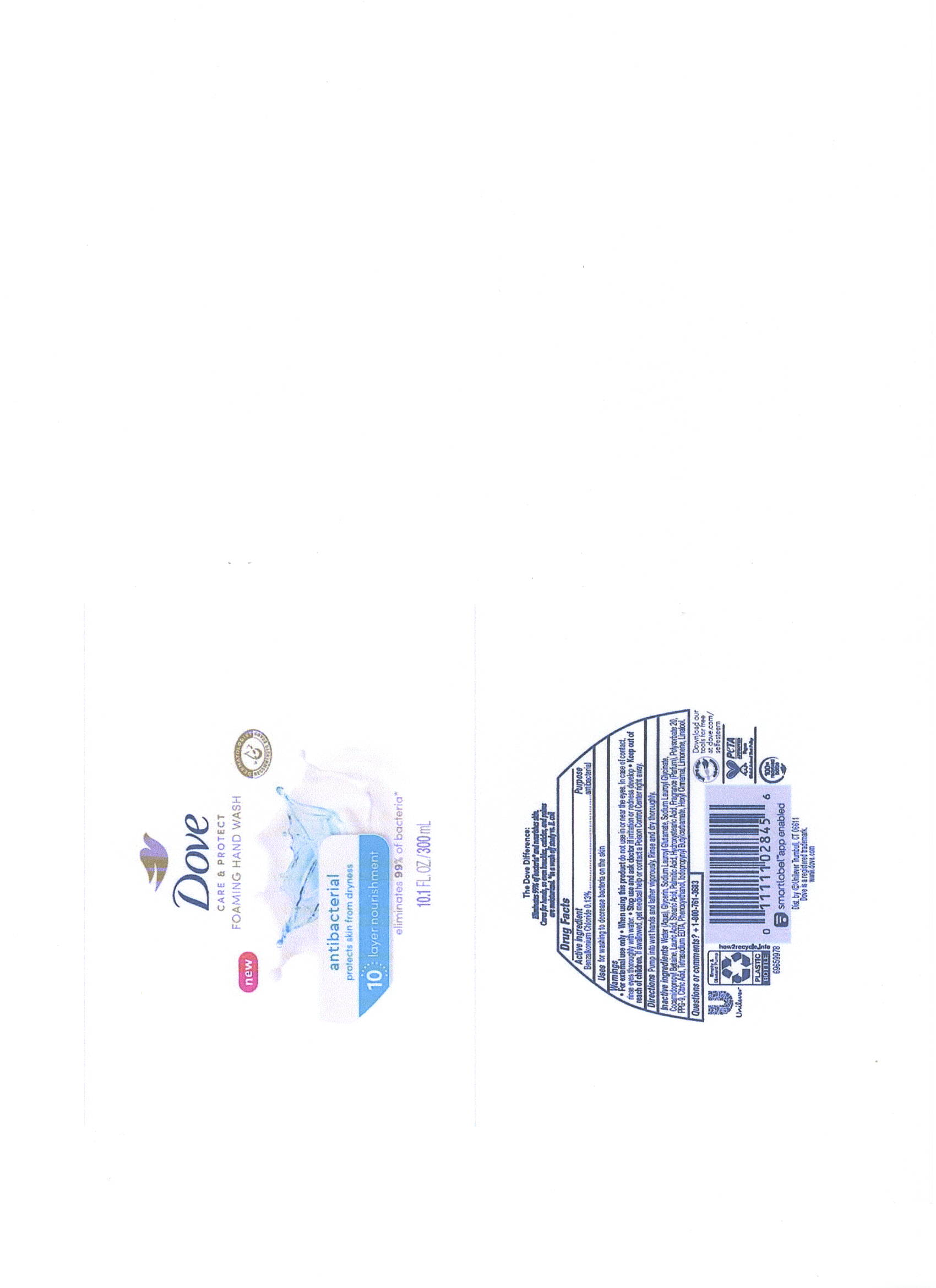 DRUG LABEL: Dove
NDC: 64942-2106 | Form: LIQUID
Manufacturer: Conopco Inc. d/b/a/ Unilever
Category: otc | Type: HUMAN OTC DRUG LABEL
Date: 20241107

ACTIVE INGREDIENTS: BENZALKONIUM CHLORIDE 1.3 mg/1 mL
INACTIVE INGREDIENTS: .ALPHA.-HEXYLCINNAMALDEHYDE; STEARIC ACID; CITRIC ACID MONOHYDRATE; WATER; GLYCERIN; COCAMIDOPROPYL BETAINE; PALMITIC ACID; LAURIC ACID; 12-HYDROXYSTEARIC ACID; POLYSORBATE 20; PPG-9; EDETATE SODIUM; PHENOXYETHANOL; IODOPROPYNYL BUTYLCARBAMATE; LIMONENE, (+)-; SODIUM LAUROYL GLUTAMATE; SODIUM LAUROYL GLYCINATE; LINALOOL, (+/-)-

Dove Care & Protect Antibacterial Foaming Hand Wash

DOVE CARE & PROTECT ANTIBACTERIAL FOAMING HAND WASH - Benzalkonium Chloride

Dove Care & Protect Antibacterial Foaming Hand Wash

Drug Facts

Active ingredient

Benzalkonium Chloride 0.13%

Purpose

Antibacterial

Uses

For washing to decrease bacteria on the skin

Warnings

• For external use only
• When using this product do not use in or near the eyes. In case of contact, rinse eyes thoroyghly with water.
• Stop use and ask doctor if irritation or redness develop

If swallowed, get medical help or contact a Poison Control Center right away.

• Keep out of reach of children except under adult supervision.

If swallowed, get medical help or contact a poison control Center right away.

Directions

Pump into wet hands and lather vigorously. Rinse and dry thoroughtly

Inactive ingredients

Water, Glycerin, Sodium Lauroyl Glutamate, Sodium Lauroyl Glycinate, Cocamidopropyl Betaine, Lauric Acid, Stearic Acid, Palmitic Acid, Hydroxystearic Acid, Fragrance (Parfum), Polysorbate 20, PPG-9, Citric Acid, Tetrasodium EDTA, Phenoxyethanol, Iodopropynyl Butylcarbamate, Hexyl Cinnamal, Limonene, Linalool.

Questions or Comments?

1-800-761-3683